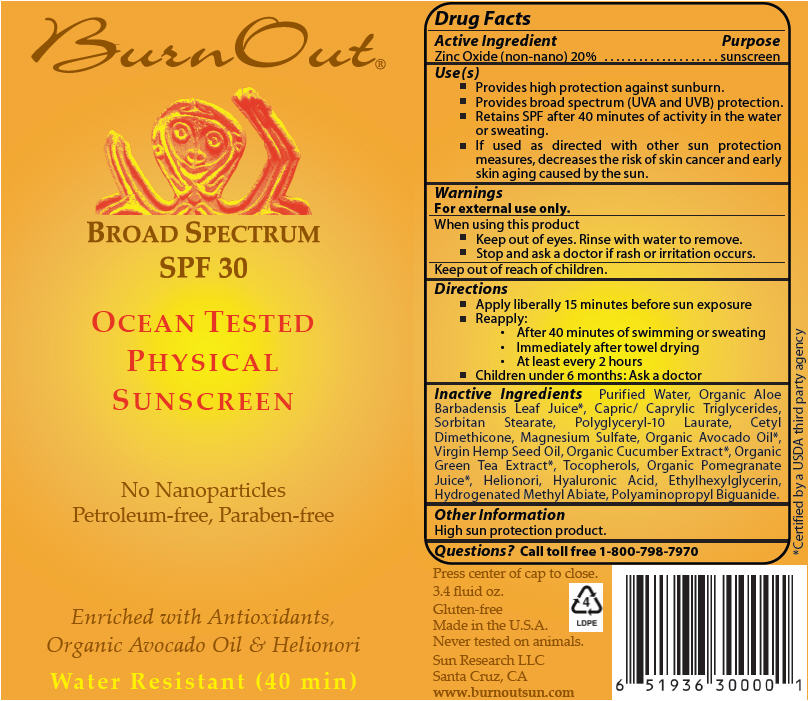 DRUG LABEL: Burn Out SPF-30 Sunscreen
NDC: 55777-0100 | Form: LOTION
Manufacturer: Sun Research LLC
Category: otc | Type: HUMAN OTC DRUG LABEL
Date: 20200121

ACTIVE INGREDIENTS: Zinc Oxide 20 g/100 mL
INACTIVE INGREDIENTS: water; aloe vera leaf; TRICAPRILIN; sorbitan monostearate; polyglyceryl-10 laurate; cetyl dimethicone 150; magnesium sulfate, unspecified form; avocado oil; cannabis sativa seed oil; green tea leaf; tocopherol; pomegranate juice; hyaluronic acid; ethylhexylglycerin; hydrogenated methyl abietate; polihexanide

Burn Out® SPF-30 Sunscreen

Drug Facts

Active Ingredient

Zinc Oxide (non-nano) 20%

Purpose

sunscreen

Use(s)

- Provides high protection against sunburn.
- Provides broad spectrum (UVA and UVB) protection.
- Retains SPF after 40 minutes of activity in the water or sweating.
- If used as directed with other sun protection measures, decreases the risk of skin cancer and early skin aging caused by the sun.

Warnings

For external use only.

When using this product

- Keep out of eyes. Rinse with water to remove.
- Stop and ask a doctor if rash or irritation occurs.

Keep out of reach of children.

Directions

- Apply liberally 15 minutes before sun exposure
- Reapply:
  - After 40 minutes of swimming or sweating
  - Immediately after towel drying
  - At least every 2 hours
- Children under 6 months: Ask a doctor

Inactive Ingredients

Purified Water, Organic Aloe Barbadensis Leaf Juice [Certified by a USDA third party agency] , Capric/ Caprylic Triglycerides, Sorbitan Stearate, Polyglyceryl-10 Laurate, Cetyl Dimethicone, Magnesium Sulfate, Organic Avocado Oil, Virgin Hemp Seed Oil, Organic Cucumber Extract, Organic Green Tea Extract, Tocopherols, Organic Pomegranate Juice, Helionori, Hyaluronic Acid, Ethylhexylglycerin, Hydrogenated Methyl Abiate, Polyaminopropyl Biguanide.

Other Information

High sun protection product.

Questions?

Call toll free 1-800-798-7970

PRINCIPAL DISPLAY PANEL - 100 ml Tube Label

Burn Out®

BROAD SPECTRUM
SPF 30

OCEAN TESTED
PHYSICAL
SUNSCREEN

No Nanoparticles
Petroleum-free, Paraben-free

Enriched with Antioxidants,
Organic Avocado Oil & Helionori

Water Resistant (40 min)